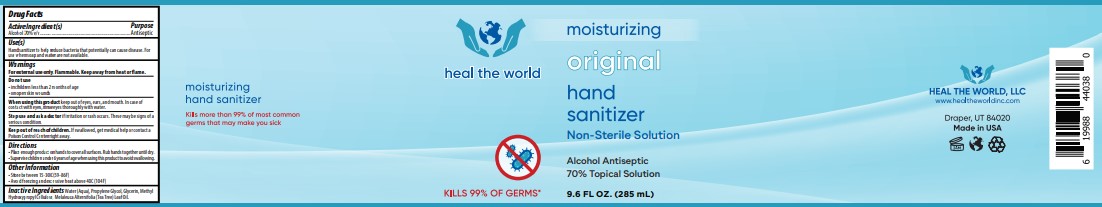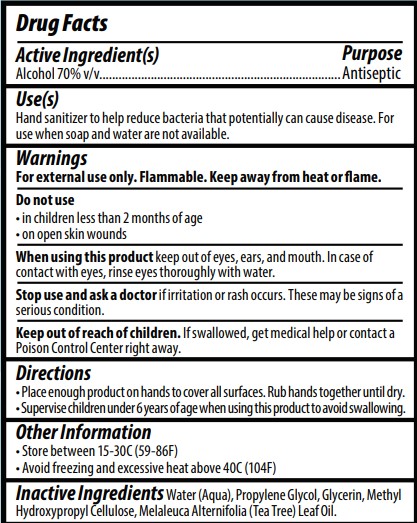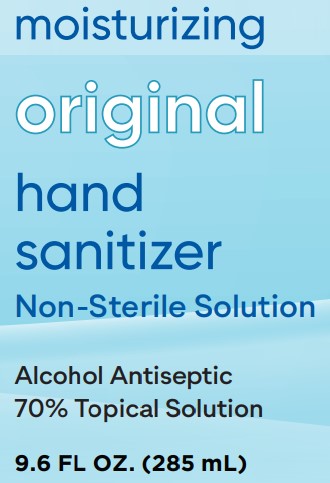 DRUG LABEL: heal the world
NDC: 73333-285 | Form: SOLUTION
Manufacturer: Nutrix International, LLC.
Category: otc | Type: HUMAN OTC DRUG LABEL
Date: 20200427

ACTIVE INGREDIENTS: ALCOHOL 0.7 mL/285 mL
INACTIVE INGREDIENTS: WATER 0.273 mL/285 mL; PROPYLENE GLYCOL 0.01 mL/285 mL; GLYCERIN 0.008 mL/285 mL; HYPROMELLOSES 0.007 mL/285 mL; TEA TREE OIL 0.002 mL/285 mL

HEAL THE WORLD

ACTIVE INGREDIENT(S)

Alcohol 70% v/v.

PURPOSE

Antiseptic, Hand Sanitizer

USE

Hand sanitizer to help reduce bacteria that potentially can cause disease. For use when soap and water are not available.

WARNINGS

For external use only. Flammable. Keep away from heat or flame.

DO NOT USE

• in children less than 2 months of age
• on open skin wounds

WHEN USING

When using this product keep out of eyes, ears, and mouth. In case of contact with eyes, rinse eyes thoroughly with water.

STOP USE

Stop use and ask a doctor if irritation or rash occurs. These may be signs of a serious condition.

Keep out of reach of children. If swallowed, get medical help or contact a Poison Control Center right away.

DIRECTIONS

• Place enough product on hands to cover all surfaces. Rub hands together until dry.
• Supervise children under 6 years of age when using this product to avoid swallowing.

OTHER INFORMATION

• Store between 15-30C (59-86F)
• Avoid freezing and excessive heat above 40C (104F)

INACTIVE INGREDIENTS

Inactive Ingredients Water (Aqua), Propylene Glycol, Glycerin, Methyl
Hydroxypropyl Cellulose, Melaleuca Alternifolia (Tea Tree) Leaf Oil.

Dosage Form

• Place enough product on hands to cover all surfaces. Rub hands together until dry.

285ml NDC: 73333-285-01

MAIN PANEL